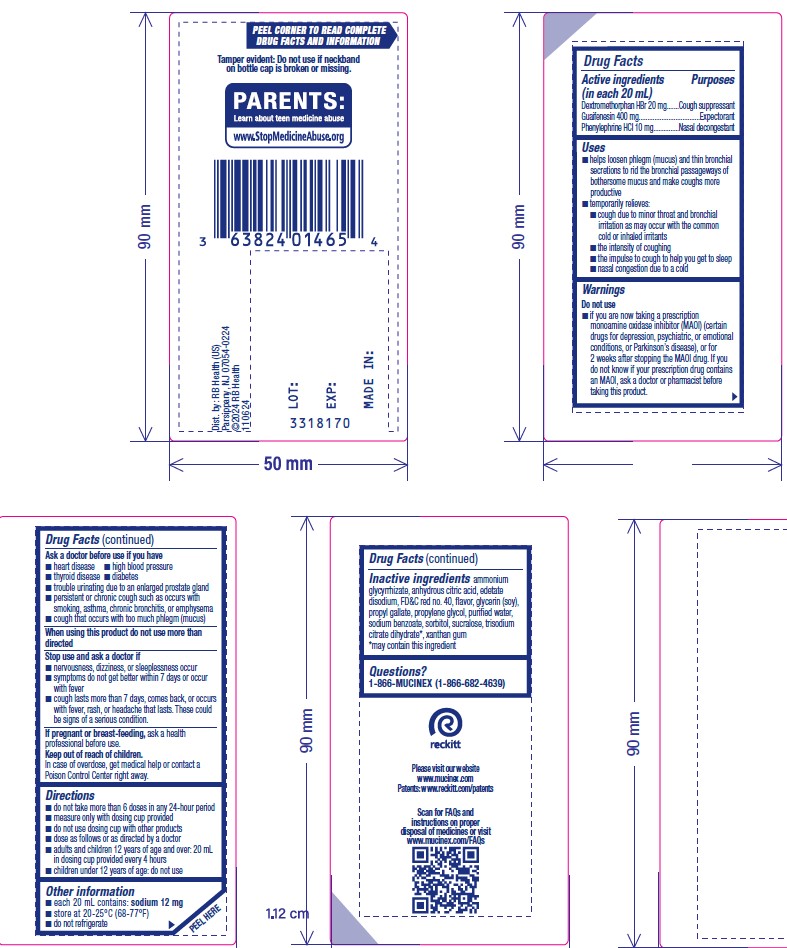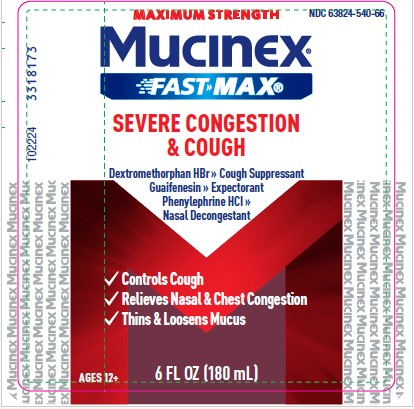 DRUG LABEL: Mucinex Fast-Max
NDC: 63824-540 | Form: SOLUTION
Manufacturer: RB Health (US) LLC
Category: otc | Type: HUMAN OTC DRUG LABEL
Date: 20250729

ACTIVE INGREDIENTS: DEXTROMETHORPHAN HYDROBROMIDE 20 mg/20 mL; GUAIFENESIN 400 mg/20 mL; PHENYLEPHRINE HYDROCHLORIDE 10 mg/20 mL
INACTIVE INGREDIENTS: AMMONIUM GLYCYRRHIZATE; ANHYDROUS CITRIC ACID; EDETATE DISODIUM; FD&C RED NO. 40; GLYCERIN; PROPYL GALLATE; PROPYLENE GLYCOL; WATER; SODIUM BENZOATE; SORBITOL; SUCRALOSE; TRISODIUM CITRATE DIHYDRATE; XANTHAN GUM

Mucinex® Fast-Max®
Severe Congestion & Cough

Drug Facts

ACTIVE INGREDIENT

PURPOSE

Active ingredients (in each 20 mL) | Purposes
Dextromethorphan HBr 20 mg | Cough suppressant
Guaifenesin 400 mg | Expectorant
Phenylephrine HCl 10 mg | Nasal decongestant

Uses

- helps loosen phlegm (mucus) and thin bronchial secretions to rid the bronchial passageways of bothersome mucus and make coughs more productive
- temporarily relieves:
  - cough due to minor throat and bronchial irritation as may occur with the common cold or inhaled irritants
  - the intensity of coughing
  - the impulse to cough to help you get to sleep
  - nasal congestion due to a cold

WARNINGS

Do not use

- if you are now taking a prescription monoamine oxidase inhibitor (MAOI) (certain drugs for depression, psychiatric, or emotional conditions, or Parkinson's disease), or for 2 weeks after stopping the MAOI drug. If you do not know if your prescription drug contains an MAOI, ask a doctor or pharmacist before taking this product.

Ask a doctor before use if you have

- heart disease
- high blood pressure
- thyroid disease
- diabetes
- trouble urinating due to an enlarged prostate gland
- persistent or chronic cough such as occurs with smoking, asthma, chronic bronchitis, or emphysema
- cough that occurs with too much phlegm (mucus)

When using this product do not use more than directed

Stop use and ask a doctor if

- nervousness, dizziness, or sleeplessness occur
- symptoms do not get better within 7 days or occur with fever
- cough lasts more than 7 days, comes back, or occurs with fever, rash, or headache that lasts. These could be signs of a serious condition.

PREGNANCY OR BREAST FEEDING

If pregnant or breast-feeding,ask a health professional before use.

Keep out of reach of children.

In case of overdose, get medical help or contact a Poison Control Center right away.

Directions

- do not take more than 6 doses in any 24-hour period
- measure only with dosing cup provided
- do not use dosing cup with other products
- dose as follows or as directed by a doctor
- adults and children 12 years of age and older: 20 mL in dosing cup provided every 4 hours
- children under 12 years of age:
  do not use

Other information

- each 20 mL contains: sodium 9 mg
- store between 20-25°C (68-77°F)
- do not refrigerate

Inactive ingredients

ammonium glycyrrhizate, anhydrous citric acid, edetate disodium, FD&C red no. 40, flavor, glycerin, propyl gallate, propylene glycol, purified water, sodium benzoate, sorbitol, sucralose, trisodium citrate dihydrate [may contain this ingredient] , xanthan gum

Questions?

1-866-MUCINEX (1-866-682-4639)

You may also report side effects to this phone number.

Dist. by: Reckitt Benckiser
Parsippany, NJ 07054-0224

PRINCIPAL DISPLAY PANEL - 180 mL Bottle Label

MAXIMUM STRENGTH
NDC 63824-540-66

Mucinex®
FAST-MAX®

SEVERE CONGESTION
& COUGH

Dextromethorphan HBr – Cough Suppressant
Guaifenesin – Expectorant
Phenylephrine HCl – Nasal Decongestant

- Controls Cough
- Relieves Nasal & Chest Congestion
- Thins & Loosens Mucus

6 FL OZ (180 mL)
FOR AGES 12+